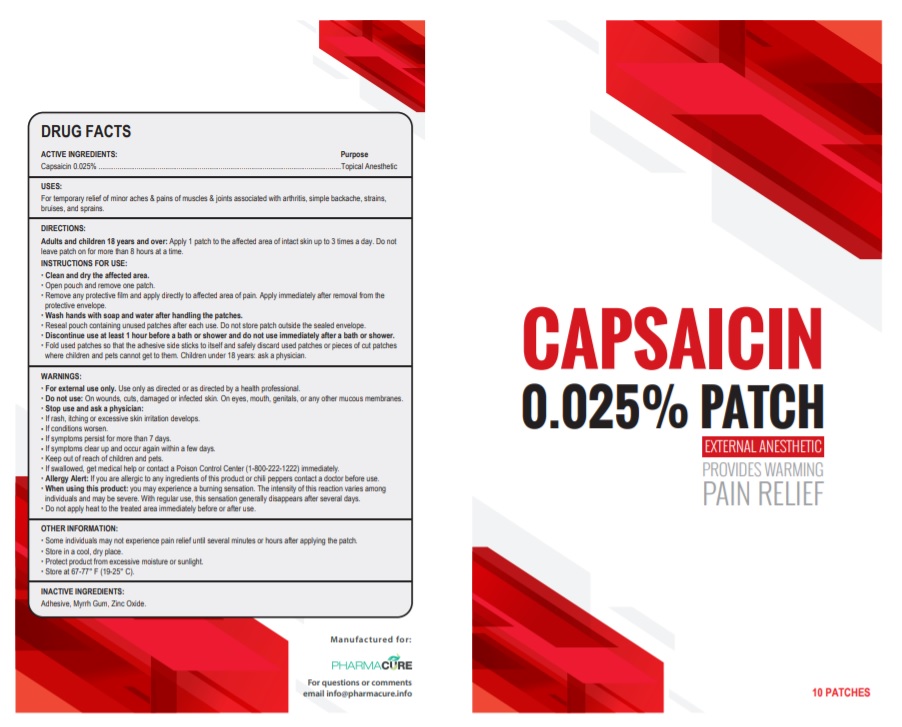 DRUG LABEL: Capsaicin
NDC: 79643-002 | Form: PATCH
Manufacturer: PHARMACURE LLC
Category: otc | Type: HUMAN OTC DRUG LABEL
Date: 20251006

ACTIVE INGREDIENTS: CAPSAICIN 0.025 g/100 g
INACTIVE INGREDIENTS: MYRRH; ZINC OXIDE

Active Ingredient

Capsaicin 0.025%

Purpose

Topical Anesthetic

Uses

Temporarily relieves mild to moderate aches and pains of muscles and joints associated with muscle soreness, strains, sprains, arthritis, simple backache, muscle stiffness, bruises.

Warnings

For external use only. Use only as directed or as directed by a health care professional.

Do not use:

• On wounds, cuts, damaged or infected skin.

• On eyes, mouth, genitals, or any other mucous membranes.

Allergy Alert: if you are allergic to capsicum or chili peppers or any inactive ingredient of this product, contact a doctor before use.

When using this product:

• You may experience a burning sensation. The intensity of this reaction varies among individuals and may be severe. With regular use, this sensation generally disappears after several days.

• Avoid contact with the eyes, lips, nose and mucous membranes.

• Do not tightly wrap or bandage the treated area.

• Do not apply heat to the treated area immediately before or after use.

Stop use and ask a physician:

• rash, itching or excessive skin irritation develops.
• conditions worsen.
• symptoms persist for more than 7 days.
• symptoms clear up and occur again within a few days.

If pregnant or breast-feeding, ask a health professional before use.

Keep out of reach of children and pets

If swallowed, get medical help or contact a Poison Control Center (1-800-222-1222) immediately.

Directions

Adults and children 18 years of age and older:

Apply 1 patch to the affected area of intact skin up to 3 times a day. Do not leave patch on for more than 8 hours at a time.

INSTRUCTIONS FOR USE :

Clean and dry the affected area.

Open pouch and remove one patch.

Remove any protective film and apply directly to affected area of pain. Apply immediately after removal from the protective envelope.

Wash hands with soap and water after handling the patches.

Reseal pouch containing unused patches after each use. Do not store patch outside the sealed envelope.

Discontinue use at least one hour prior to bath, shower, or swimming; do not use immediately after bath, shower, or swimming.

Fold used patches so that the adhesive side sticks to itself and safely discard used patches or pieces of cut patches where children and pets cannot get to them.

Children under 18 years: Ask a physician

Inactive ingredients

Adhesive, myrrh gum, zinc oxide.

Other information

Some individuals may not experience pain relief until several minutes or hours after applying the patch. Store in a cool, dry place. Protect the product from excessive moisture or sunlight. Store at 67-77°F (19-25°C).